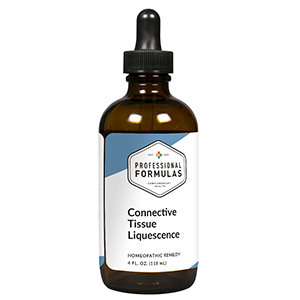 DRUG LABEL: Connective Tissue Liquescence
NDC: 63083-3024 | Form: LIQUID
Manufacturer: Professional Complementary Health Formulas
Category: homeopathic | Type: HUMAN OTC DRUG LABEL
Date: 20190815

ACTIVE INGREDIENTS: BOVINE TYPE I COLLAGEN (SKIN) 3 [hp_X]/118 mL; HYPERICUM PERFORATUM WHOLE 3 [hp_X]/118 mL; BOS TAURUS LIGAMENT 3 [hp_X]/118 mL; RUTA GRAVEOLENS FLOWERING TOP 3 [hp_X]/118 mL; BOS TAURUS NERVE 3 [hp_X]/118 mL; BRYONIA ALBA ROOT 4 [hp_X]/118 mL; ARNICA MONTANA WHOLE 6 [hp_X]/118 mL; BOS TAURUS BONE MARROW 6 [hp_X]/118 mL; CHONDROITIN SULFATE (BOVINE) 6 [hp_X]/118 mL; EUPATORIUM PERFOLIATUM FLOWERING TOP 6 [hp_X]/118 mL; GLUCOSAMINE SULFATE 6 [hp_X]/118 mL; MAGNESIUM 6 [hp_X]/118 mL; MANGANESE 6 [hp_X]/118 mL; TOXICODENDRON PUBESCENS LEAF 6 [hp_X]/118 mL; SILICON DIOXIDE 6 [hp_X]/118 mL
INACTIVE INGREDIENTS: ALCOHOL; WATER

T24

ACTIVE INGREDIENTS

Collagen 3X
Hypericum perforatum 3X
Ligament 3X
Ruta graveolens 3X
Synovium 3X
Bryonia 4X
Arnica montana 6X
Bone marrow 6X
Chondroitin sulfate 6X
Eupatorium perfoliatum 6X
Glucosamine sulfate 6X
Magnesium metallicum 6X
Manganum metallicum 6X
Rhus toxicodendron 6X
Silicea 6X

QUESTIONS

Professional Formulas

PO Box 2034 Lake Oswego, OR 97035

INDICATIONS

For the temporary relief of minor aches and pains in the bones, muscles, or joints.*

PURPOSE

*Claims based on traditional homeopathic practice, not accepted medical evidence. Not FDA evaluated.

WARNINGS

In case of overdose, get medical help or contact a poison control center right away.

Keep out of the reach of children.

PREGNANCY OR BREAST FEEDING

If pregnant or breastfeeding, ask a healthcare professional before use.

DIRECTIONS

Place drops under tongue 30 minutes before/after meals. Adults and children 12 years and over: Take one full dropper up to 2 times per day. Consult a physician for use in children under 12 years of age.

OTHER INFORMATION

Tamper resistant. If seal is broken, do not use. After opening, close container tightly and store at room temperature away from heat.

INACTIVE INGREDIENTS

20% ethanol, purified water.

LABEL

Est 1985

Professional Formulas

Complementary Health

Connective Tissue Liquescence

Homeopathic Remedy

4 FL. OZ. (118 mL)